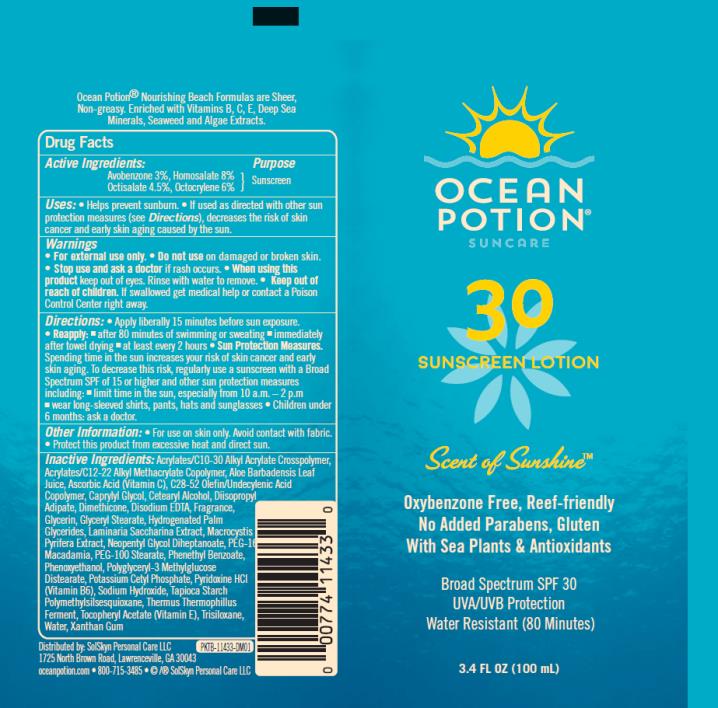 DRUG LABEL: Ocean Potion SPF30 Sunscreen
NDC: 70281-504 | Form: LOTION
Manufacturer: SolSkyn Personal Care LLC
Category: otc | Type: HUMAN OTC DRUG LABEL
Date: 20180221

ACTIVE INGREDIENTS: AVOBENZONE 3 mg/100 mg; HOMOSALATE 8 mg/100 mg; OCTISALATE 4.5 mg/100 mg; OCTOCRYLENE 6 mg/100 mg
INACTIVE INGREDIENTS: CARBOMER INTERPOLYMER TYPE A (55000 CPS); ALOE VERA LEAF; ASCORBIC ACID; CAPRYLYL GLYCOL; CETOSTEARYL ALCOHOL; DIISOPROPYL ADIPATE; DIMETHICONE; EDETATE DISODIUM ANHYDROUS; GLYCERIN; GLYCERYL MONOSTEARATE; HYDROGENATED PALM GLYCERIDES; LAMINARIA SACCHARINA EXTRACT; MACROCYSTIS PYRIFERA; NEOPENTYL GLYCOL DIHEPTANOATE; PEG-16 MACADAMIA GLYCERIDES; PEG-100 STEARATE; PHENETHYL BENZOATE; PHENOXYETHANOL; POTASSIUM CETYL PHOSPHATE; PYRIDOXINE HYDROCHLORIDE; SODIUM HYDROXIDE; THERMUS THERMOPHILUS LYSATE; .ALPHA.-TOCOPHEROL ACETATE; TRISILOXANE; WATER; XANTHAN GUM

OP SPF 30 100ml

OP SPF 30 Lotion

Active Ingredients

Avobenzone 3%, Homosalate 8%, Octisalate 4.5%, Octocrylene 6%

Purpose

Sunscreen

Uses

- helps prevent sunburn
- if used as directed with other sun protection measures (see Directions), decreases the risk of skin cancer and early skin aging caused by the sun

Warnings

- For external use only
- Flammable: keep away from fire or flame.

When using this product keep out of eyes.

Rinse with water to remove.

Keep out of reach of children.

If product is swallowed, get medical help or contact a Poison Control Center right away.

Directions

- apply liberally 15 minutes before sun exposure
- re-apply:
  • after 80 minutes of swimming or sweating
  • immediately after towel drying
  • at least every 2 hours

Sun Protection Measures. Spending time in the sun increases your risk of skin cancer and early skin aging. To decrease this risk, regularly use a sunscreen with broad spectrum SPF of 15 or higher and other sun protection measures including:

- limit time in the sun, especially from 10 a.m.-2 p.m.
- wear long-sleeved shirts, pants, hats and sunglasses
- children under 6 months: ask a doctor

Other information

- protect this product from excessive heat and direct sun
- For use on skin only. Avoid contact with fabric.

Inactive Ingredients

Acrylates/C10-30 Alkyl Acrylate Crosspolymer, Acrylates/C12-22 Alkyl Methacrylate Copolymer, Aloe Barbadensis Leaf Juice, Ascorbic Acid (Vitamin C), C28-52 Olefin/Undecylenic Acid Copolymer, Caprylyl Glycol, Cetearyl Alcohol, Diisopropyl Adipate, Dimethicone, Disodium EDTA, Fragrance, Glycerin, Glyceryl Stearate, Hydrogenated Palm Glycerides, Laminaria Saccharina Extract, Macrocystis Pyrifera Extract, Neopentyl Glycol Diheptanoate, PEG-16 Macadamia, PEG-100 Stearate, Phenethyl Benzoate, Phenoxyethanol, Polyglyceryl-3 Methylglucose Distearate, Potassium Cetyl Phosphate, Pyridoxine HCl (Vitamin B6), Sodium Hydroxide, Tapioca Starch Polymethylsilsesquioxane, Thermus Thermophillus Ferment, Tocopheryl Acetate (Vitamin E), Trisiloxane, Water, Xanthan Gum

Questions or comments?

www.oceanpotion.com call toll-free 1-800-715-3485

MAY STAIN SOME FABRICS, PLASTICS AND WOOD SURFACES.

PRINCIPAL DISPLAY PANEL

OCEAN
POTION
SUNCARE
30
SUNSCREEN LOTION
Scent of sunshine
3.4 FL OZ (100 mL)